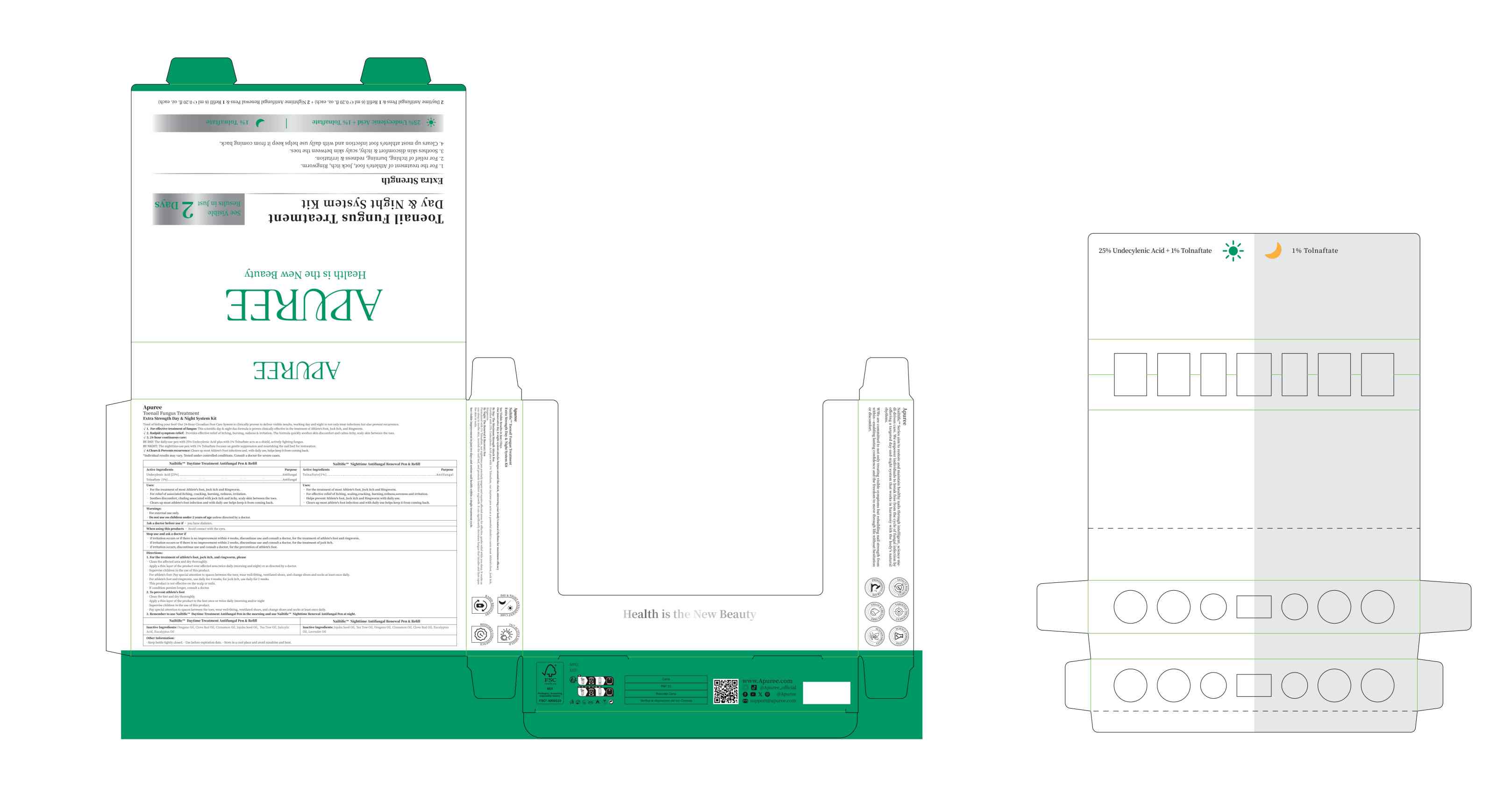 DRUG LABEL: Nailtific Daytime Treatment Antifungal Pen  Refill
NDC: 84167-012 | Form: LIQUID
Manufacturer: Guangzhou Meixi Biotechnology Co., Ltd.
Category: otc | Type: HUMAN OTC DRUG LABEL
Date: 20260129

ACTIVE INGREDIENTS: UNDECYLENIC ACID 1.5 g/6 mL; TOLNAFTATE 0.06 g/6 mL
INACTIVE INGREDIENTS: SALICYLIC ACID; CINNAMON OIL; CLOVE OIL; EUCALYPTUS OIL; JOJOBA OIL; OREGANO LEAF OIL; TEA TREE OIL

2

UNDECYLENIC ACID,TOLNAFTATE

3

OREGANO OIL,CLOVE BUD OIL,CINNAMON OIL,JOJOBA SEED OIL,TEA TREE OIL,SALICYLIC ACID,EUCALYPTUS OIL

4

warnings section

5

6ml 0.2fl

6

keep out of reach of children section

7

Used to remove fungi from the skin or hands and feet

8

Apply to the affected area every 2 days